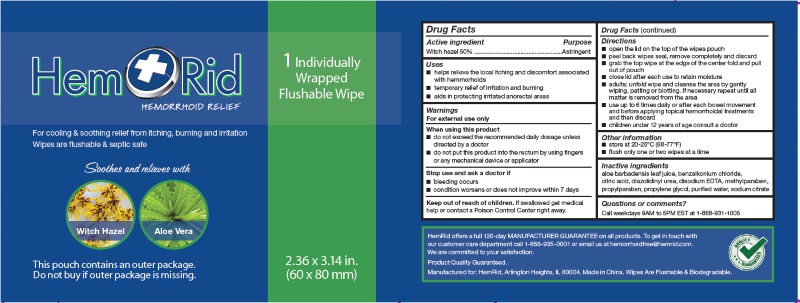 DRUG LABEL: HemRid MEDICATED WIPES
NDC: 71430-100 | Form: SWAB
Manufacturer: BELLIGADRIA SOLLUTIONS LLC
Category: otc | Type: HUMAN OTC DRUG LABEL
Date: 20160104

ACTIVE INGREDIENTS: WITCH HAZEL 0.5 g/1 g
INACTIVE INGREDIENTS: ALOE VERA LEAF; BENZALKONIUM; CITRIC ACID MONOHYDRATE; DIAZOLIDINYL UREA; DISODIUM COCOAMPHODIACETATE; METHYLPARABEN; PROPYLPARABEN; PROPYLENE GLYCOL; WATER; SODIUM CITRATE

HEMRID medicated wipes

Active ingredient

Witch hazel 50%

Purpose

Astringent

Uses

1. helps relieve the local itching and discomfort associated with hemmorhoids
2. temporary relief of irritation and burning
3. aids in protecting irritated anorectal areas

Warnings

For external use only. Avoid contact with eyes.

When using this product

- do not exceed the recommended daily dosage unless directed by a doctor
- do not put this product into the rectum by using fingers or any mechanical device or applicator

Stop use and ask doctor if

- bleeding occurs
- condition worsens or does not improve within 7 days

Keep out of reach of children

If swallowed, get medical help or contact a Pposion Control Center right away. (1-800-222-1222)

Directions

- open the lid on the top of the wipes pouch
- peel back wipes seal, remove completely and discard
- grab the top wipe at the edge of the center fold and pull out of pouch
- close lid after each use to retain moisture
- adults: unfold wipe and cleanse the area by gently wiping, patting or blotting. If necessary repeat until all matter is removed from the area
- use up to 6 times daily or after each bowel movement and before applying topical hemorrhoidal treatments and then discard
- children under 12 years of age consult a doctor

Other information

- Store at 20-25°C (68-77°F)
- Flush only one or two wipes at a time

Iactive ingredients

Puried Water, Glycerin, Propylene Glycol, Aloe Barbadensis Leaf Juice,
Benzalknum Chloride, Diazolidiny Urea, Methyl Paraben, Propyl paraben,
Sodium Citrate, Citric Acid, Disodium EDTA

Questions or Comments

Call weekdays 9AM to 5PM EST at 1-888-931-1005

Principal Display Panel

HemRid
126E Wing St, Suite #355, Arlington Heights IL 60005
www.HemRid.com
888-931-1005
info@hemrid.com
Made in China.
Flushable & Biodegradable, Single Use